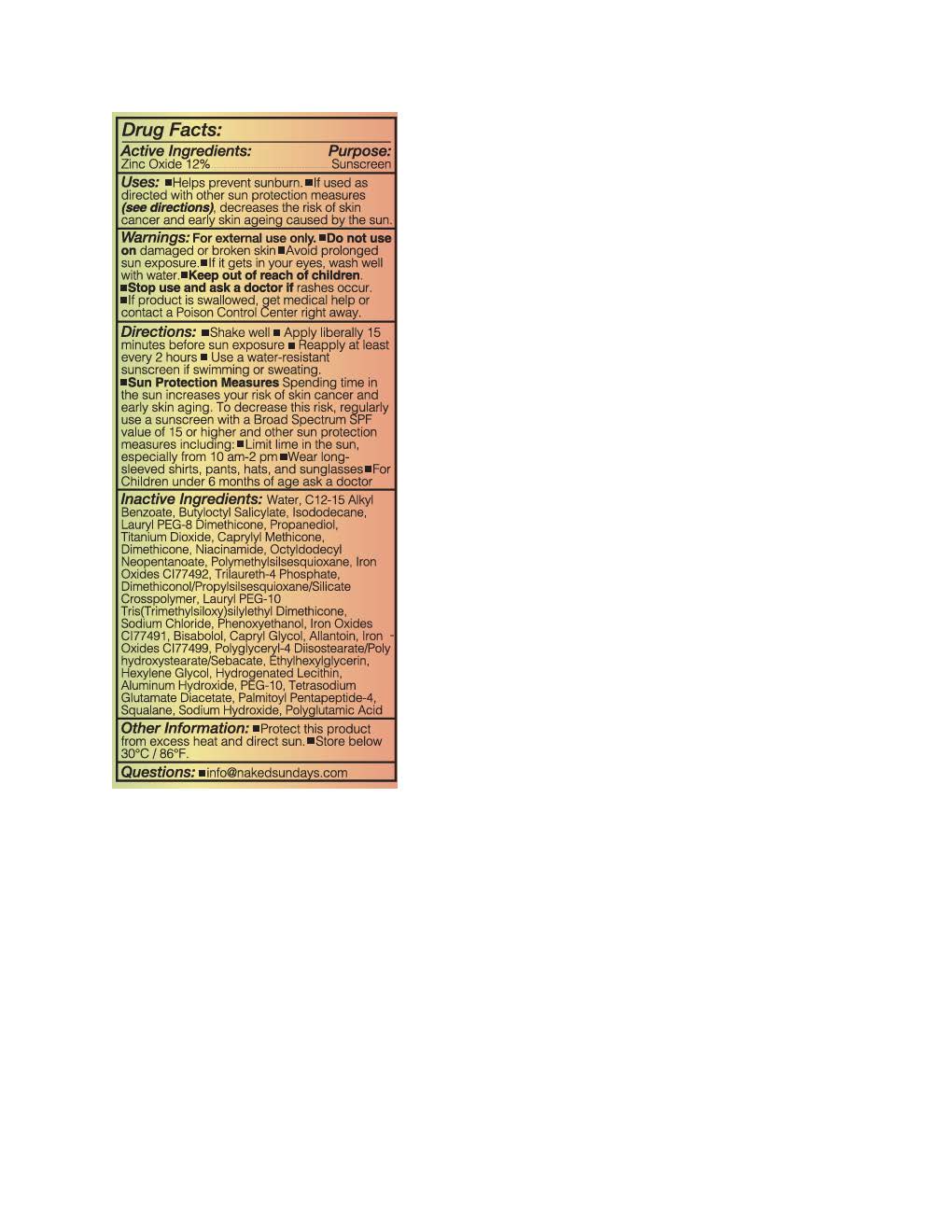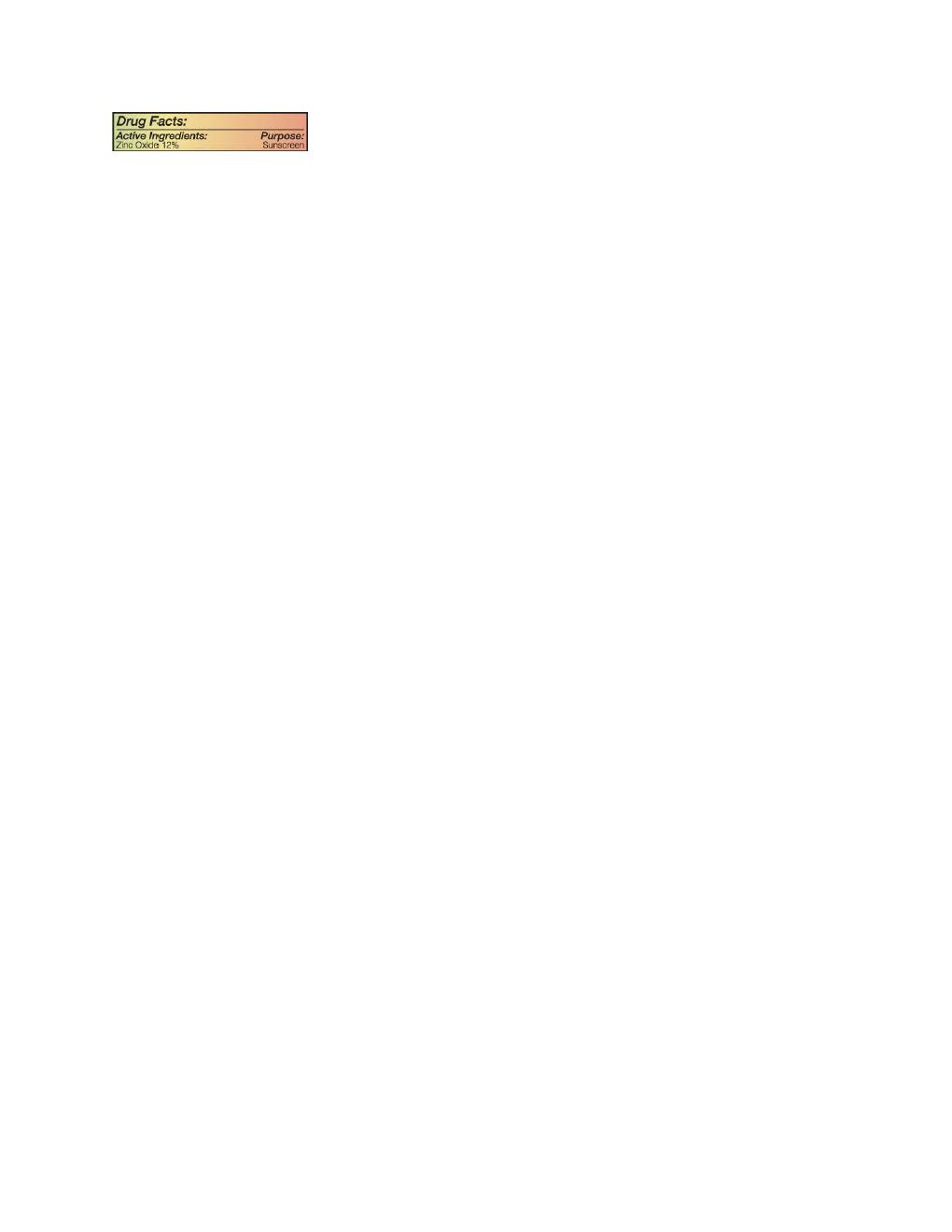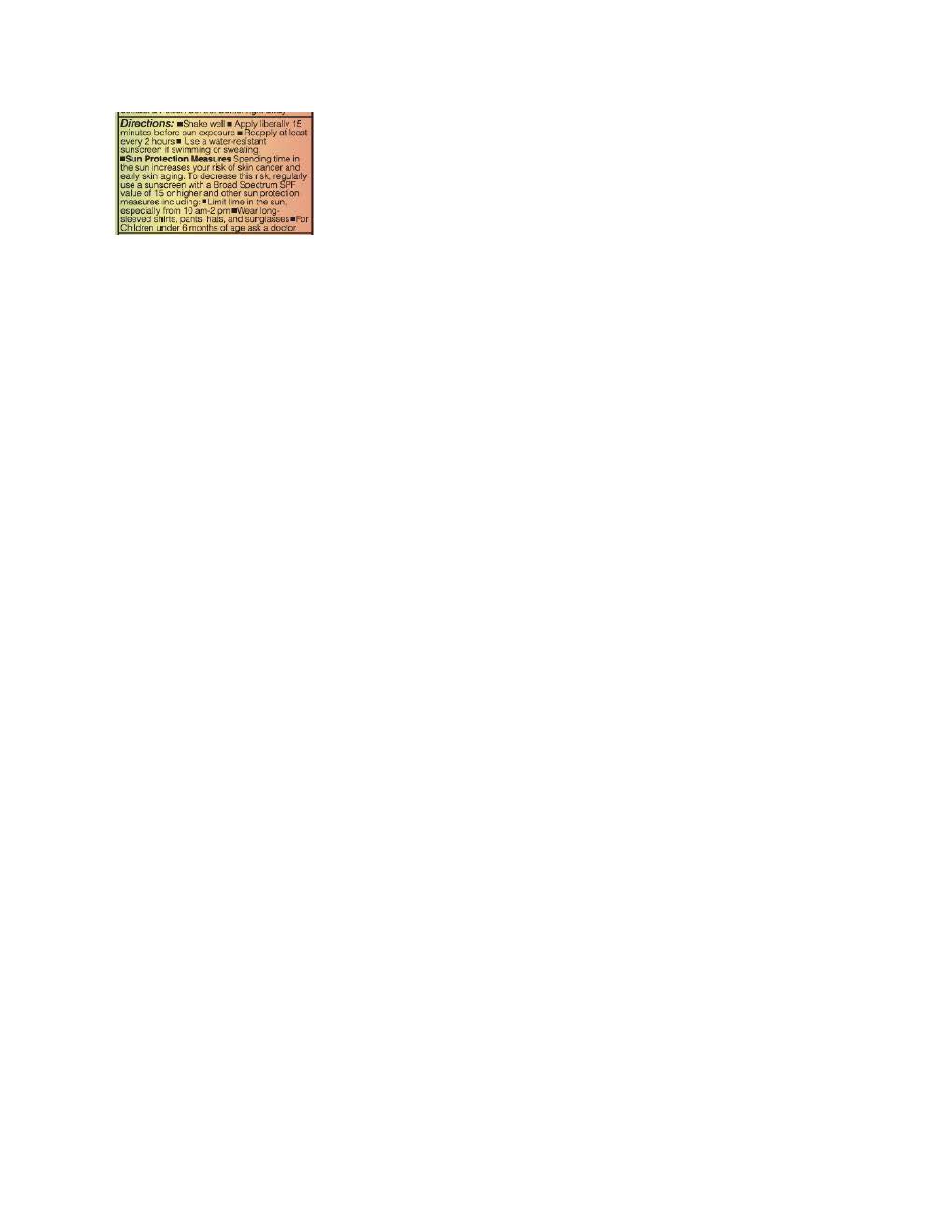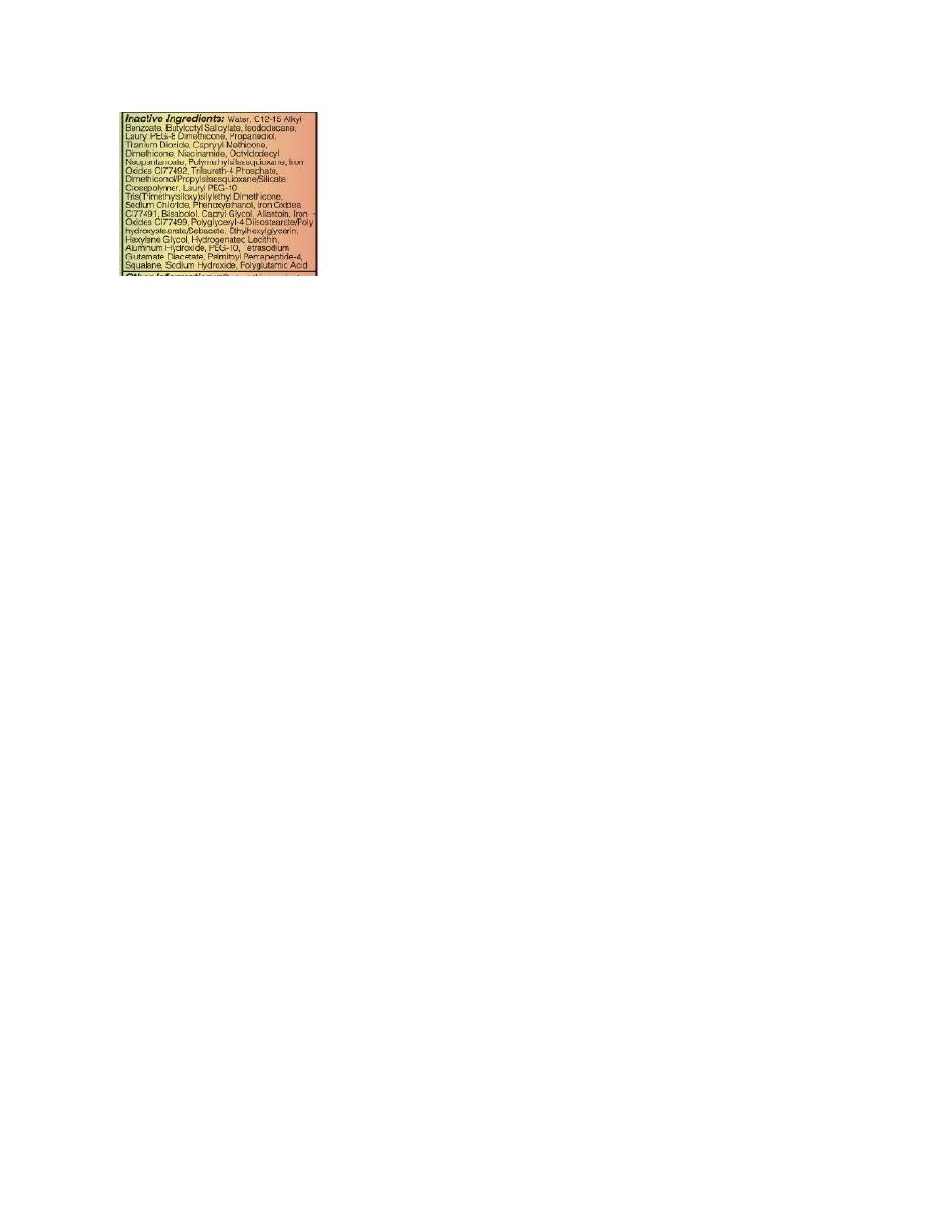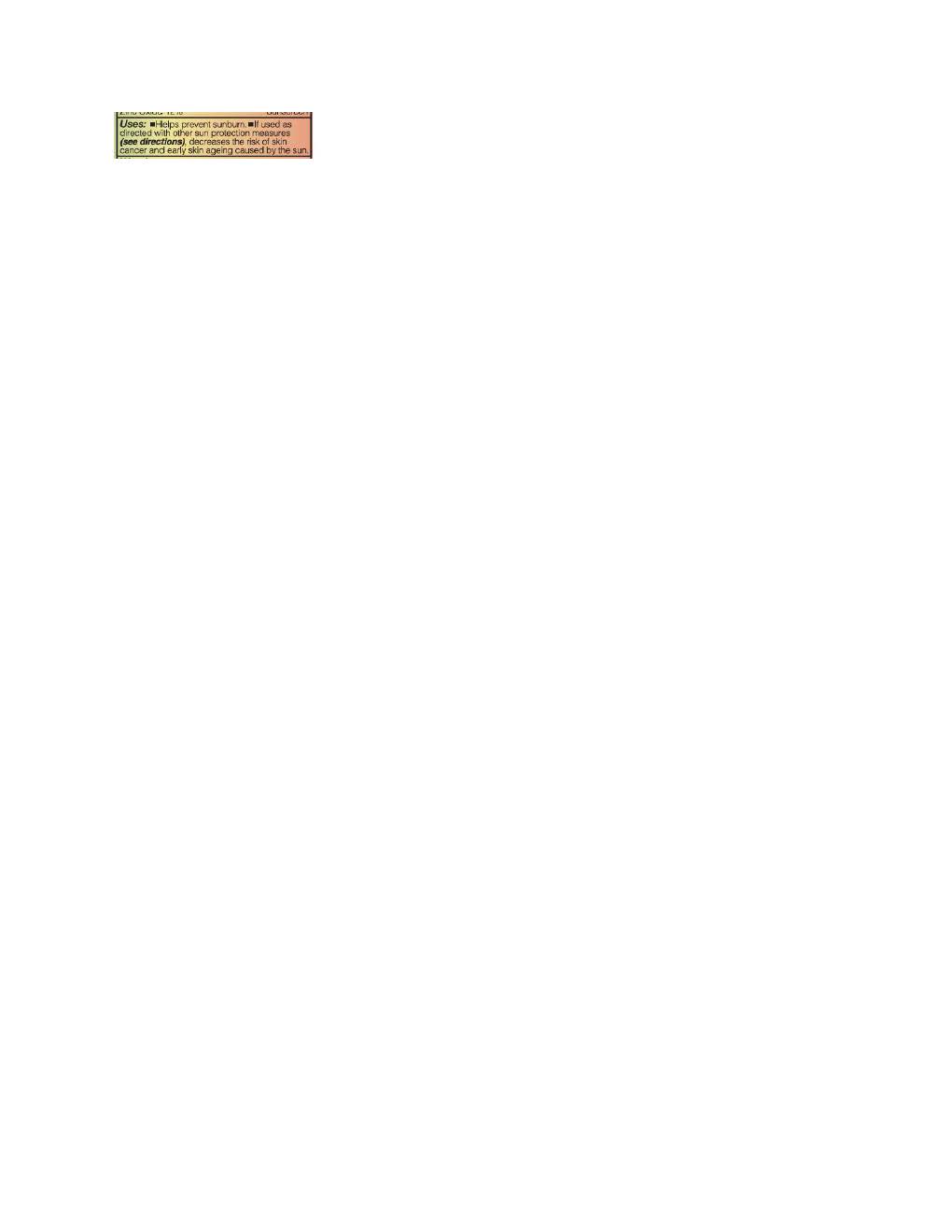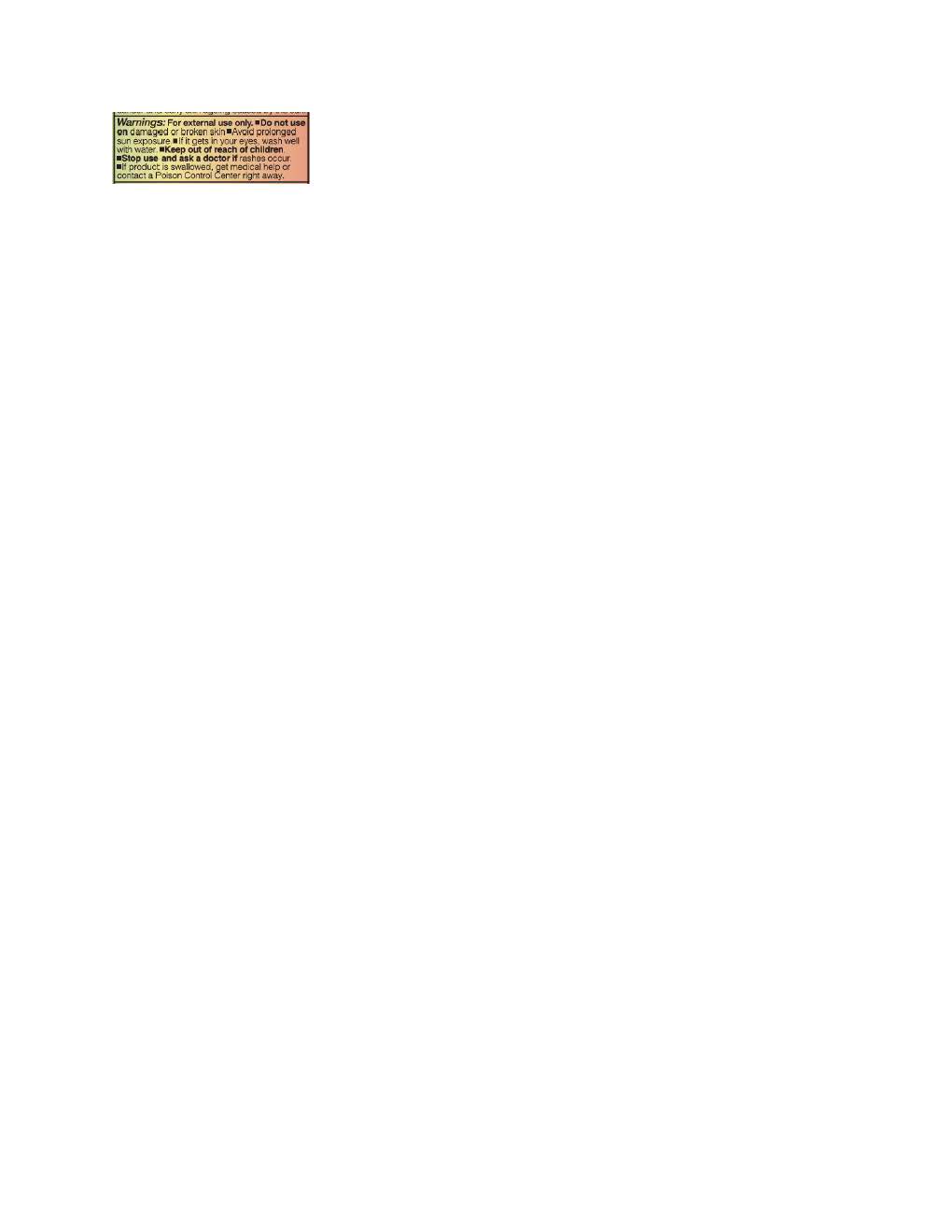 DRUG LABEL: Naked Sundays BeautyScreen Peptide Foundation Tint
NDC: 81104-664 | Form: LOTION
Manufacturer: Naked Sundays
Category: otc | Type: HUMAN OTC DRUG LABEL
Date: 20251104

ACTIVE INGREDIENTS: ZINC OXIDE 132 mg/1 mL
INACTIVE INGREDIENTS: LAURYL PEG-8 DIMETHICONE (300 CPS); FERRIC OXIDE YELLOW; ALKYL (C12-15) BENZOATE; POLYMETHYLSILSESQUIOXANE (4.5 MICRONS); DIMETHICONE; WATER; NIACINAMIDE; ETHYLHEXYLGLYCERIN; HEXYLENE GLYCOL; TRILAURETH-4 PHOSPHATE; DIMETHICONOL/PROPYLSILSESQUIOXANE/SILICATE CROSSPOLYMER (450000000 MW); PROPANEDIOL; TETRASODIUM GLUTAMATE DIACETATE; FERRIC OXIDE RED; SODIUM CHLORIDE; PHENOXYETHANOL; BUTYLOCTYL SALICYLATE; OCTYLDODECYL NEOPENTANOATE; ISODODECANE; .ALPHA.-BISABOLOL, (+)-; ALLANTOIN

Naked Sundays BeautyScreen Peptide Foundation Tint